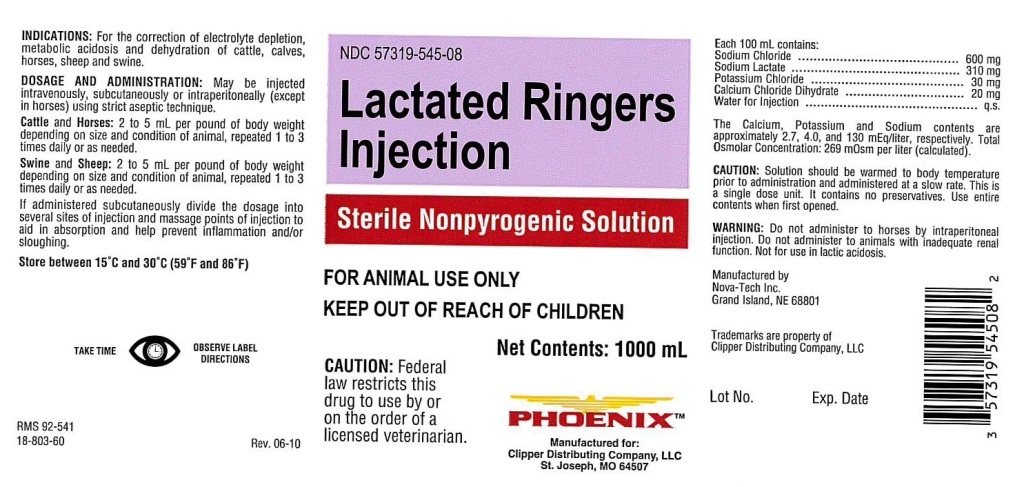 DRUG LABEL: Lactated Ringers
NDC: 57319-545 | Form: INJECTION, SOLUTION
Manufacturer: Clipper
Category: animal | Type: PRESCRIPTION ANIMAL DRUG LABEL
Date: 20240424

ACTIVE INGREDIENTS: SODIUM CHLORIDE 600 mg/100 mL; SODIUM LACTATE 310 mg/100 mL; POTASSIUM CHLORIDE 30 mg/100 mL; CALCIUM CHLORIDE 20 mg/100 mL

Lactated Ringers Injection

INDICATIONS:

For the correction of electrolyte depletion,
metabolic acidosis and dehydration of cattle, calves,
horses, sheep and swine.

DOSAGE AND ADMINISTRATION:

May be injected
intravenously, subcutaneously or intraperitoneally (except
in horses) using strict aseptic technique.

Cattle and Horses: 2 to 5 mL per pound of body weight
depending on size and condition of animal, repeated 1 to 3
times daily or as needed.

Swine and Sheep: 2 to 5 mL per pound of body weight
depending on size and condition of animal, repeated 1 to 3
times daily or as needed.

If administered subcutaneously divide the dosage into
several sites of injection and massage points of injection to
aid in absorption and help prevent inflammation and/or
sloughing.

STORAGE AND HANDLING

Store between 15°C and 30°C (59°F and 86°F)

VETERINARY INDICATIONS

FOR ANIMAL USE ONLY

KEEP OUT OF REACH OF CHILDREN

Sterile Nonpyrogenic Solution

KEEP OUT OF REACH OF CHILDREN

CAUTION:

Federal law restricts this drug to use by or on the order of a licensed veterinarian.

DOSAGE FORMS AND STRENGTHS

Each 100 mL contains:
Sodium Chloride ............................... 600 mg
Sodium Lactate ................................ 310 mg
Potassium Chloride ............................. 30 mg
Calcium Chloride Dihydrate ................. 20 mg
Water for Injection ................................ q.s.

The Calcium, Potassium and Sodium contents are
approximately 2.7, 4.0, and 130 mEq/liter, respectively. Total
Osmolar Concentration: 269 mOsm per liter (calculated).

CAUTION:

Solution should be warmed to body temperature
prior to administration and administered at a slow rate. This is
a single dose unit. It contains no preservatives. Use entire
contents when first opened.

WARNING:

Do not administer to horses by intraperitoneal
injection. Do not administer to animals with inadequate renal
function. Not for use in lactic acidosis.

PRECAUTIONS

TAKE TIME OBSERVE LABEL DIRECTIONS

INFORMATION FOR OWNERS/CAREGIVERS

RMS 92-541

18-803-60

Rev. 06-10

NDC 57319-545-08

Net Contents: 1000 mL

Manufactured for:
Clipper Distributing Company, LLC
St. Joseph, MO 64507

Manufactured by
Nova-Tech Inc.
Grand Island, NE 68801

Trademarks are property of
Clipper Distributing Company, LLC

Lot No.

Exp. Date